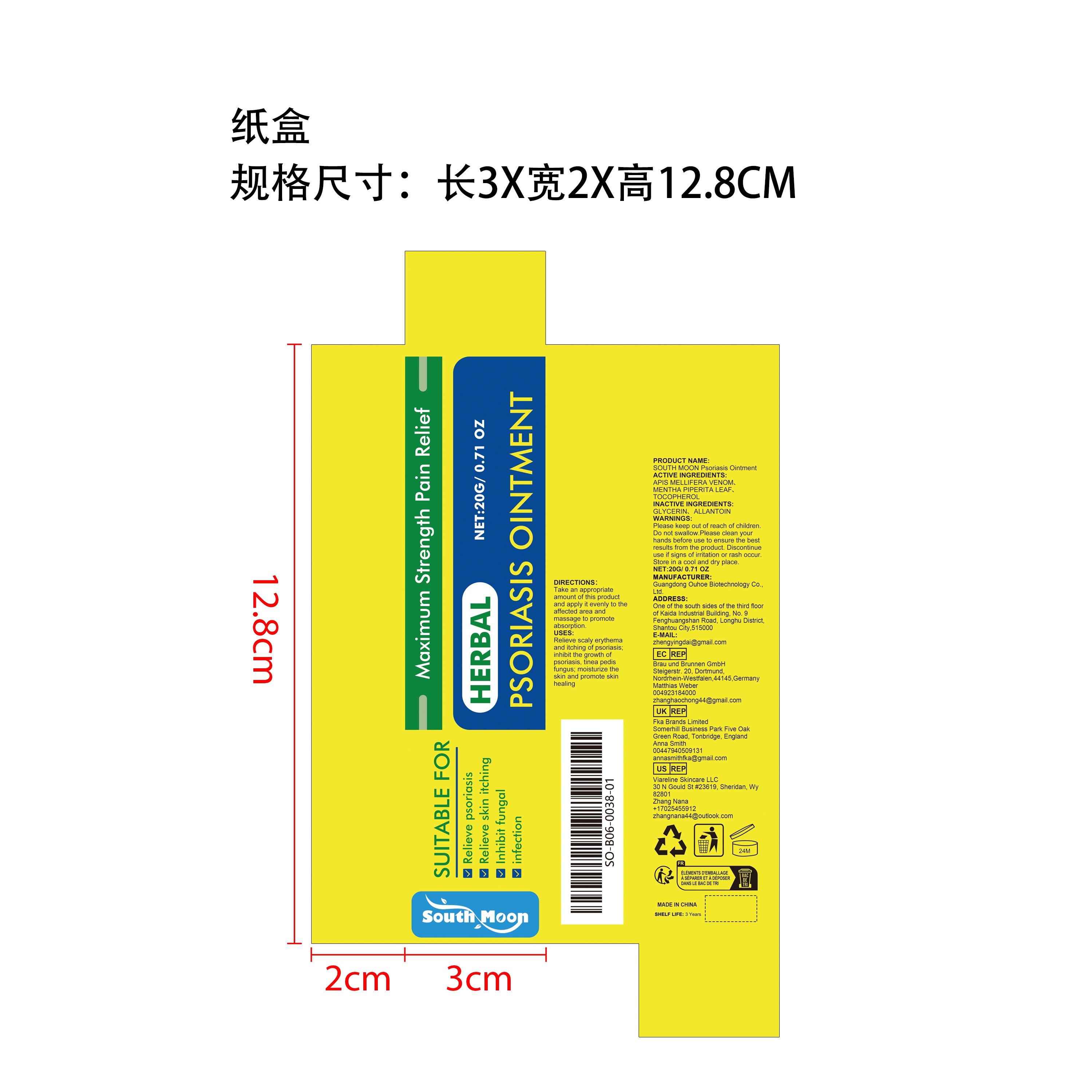 DRUG LABEL: SOUTH MOON Psoriasis
NDC: 84744-061 | Form: CREAM
Manufacturer: Guangdong Ouhoe Biotechnology Co., Ltd.
Category: otc | Type: HUMAN OTC DRUG LABEL
Date: 20241024

ACTIVE INGREDIENTS: TOCOPHEROL 3 g/20 g; APIS MELLIFERA VENOM 6 g/20 g; MENTHA PIPERITA LEAF 2 g/20 g
INACTIVE INGREDIENTS: GLYCERIN 3 g/20 g; ALLANTOIN 6 g/20 g

ACTIVE INGREDIENTS

APIS MELLIFERA VENOM、MENTHA PIPERITA LEAF、 TOCOPHEROL

purpose

Relieve scaly erythema and itching of psoriasis; inhibit the growth ofpsoriasis, tinea pedisfungus; moisturize the skin and promote skin healing

use

Take an appropriate amount of this product and apply it evenly to the affected area and massage to promote absorption.

WARNINGS

Please keep out of reach of children. Do not swallow.Please clean your hands before use to ensure the best results from the product. Discontinue use if signs of irritation or rash occur. Store in a cool and dry place.

KEEP OUT OF REACH OF CHILDREN

Please keep out of reach of children. Do not swallow.

stop use

Discontinue use if signs of irritation or rash occur.

Do not use

Discontinue use if signs of irritation or rash occur.

STORAGE AND HANDLING

Store in a cool and dry place.

INACTIVE INGREDIENT

GLYCERIN、ALLANTOIN